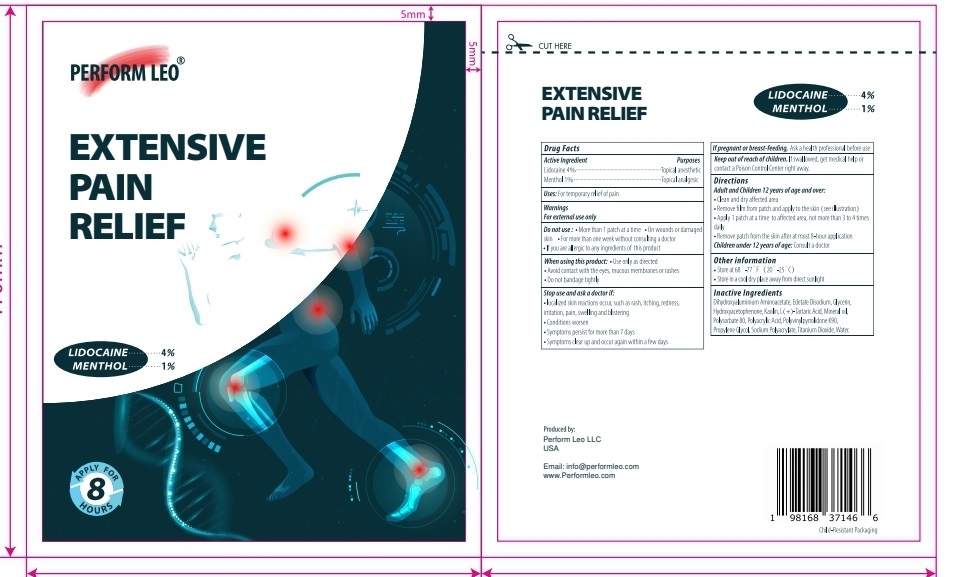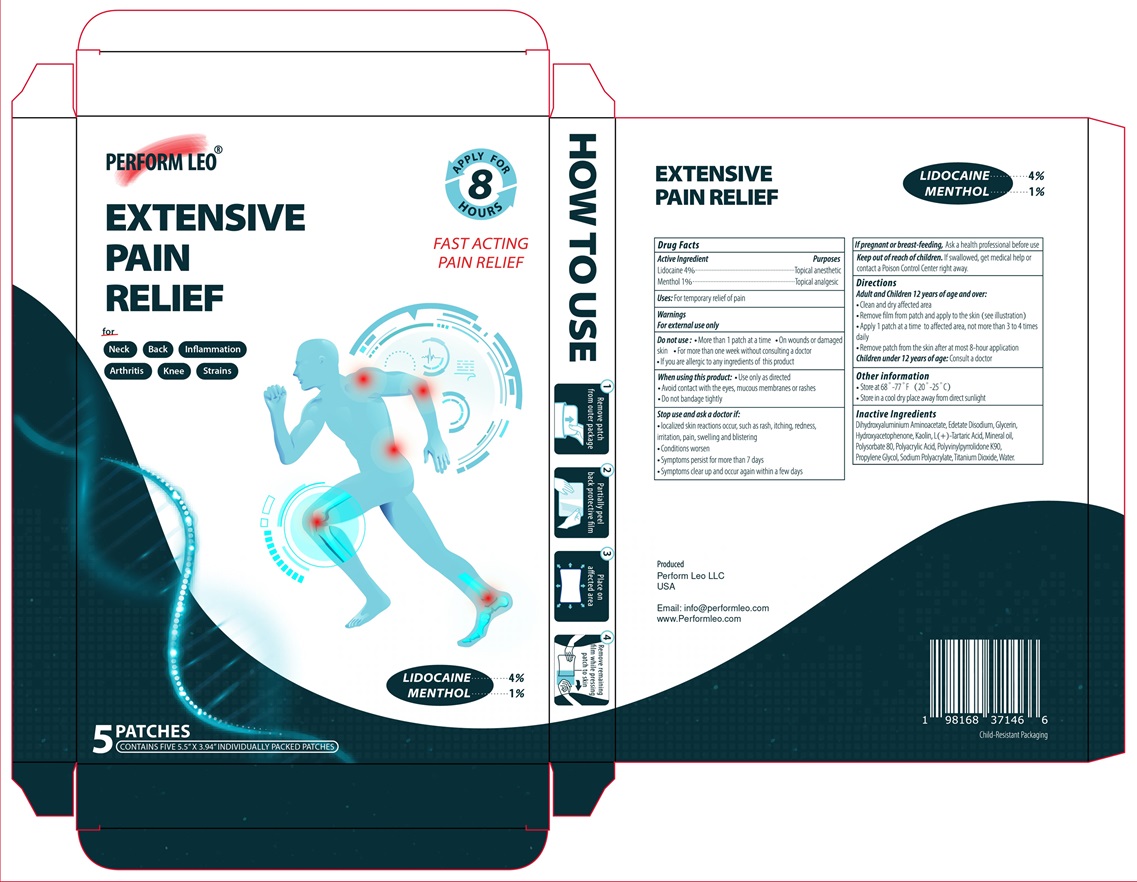 DRUG LABEL: PERFORM LEO  EXTENSIVE PAIN RELIEF
NDC: 84410-001 | Form: PATCH
Manufacturer: PERFORM LEO LLC
Category: otc | Type: HUMAN OTC DRUG LABEL
Date: 20251015

ACTIVE INGREDIENTS: LIDOCAINE 4 g/100 g; MENTHOL 1 g/100 g
INACTIVE INGREDIENTS: DIHYDROXYALUMINUM AMINOACETATE; EDETATE DISODIUM; GLYCERIN; HYDROXYACETOPHENONE; KAOLIN; TARTARIC ACID; MINERAL OIL; POLYSORBATE 80; POLYACRYLIC ACID (250000 MW); POVIDONE K90; PROPYLENE GLYCOL; SODIUM POLYACRYLATE (2500000 MW); TITANIUM DIOXIDE; WATER

Active Ingredient Purpose

Lidocaine 4% Topical anesthetic

Menthol 1% Topical analgesic

Uses

For the temporary pain relief

Warnings

For external use only

Do not use

- More than one patch at a time
- On wounds or damaged skin
- For more than one week without consulting a doctor
- If you are allergic to any ingredients of this product

When using this product

- Use only as directed
- Avoid contact with the eyes, mucous membranes or rashes
- Do not bandage tightly

Stop use and ask a doctor if :

- localized skin reactions occur, such as rash, itching, redness, irritation, pain, swelling and blistering
- conditions worsen
- symptoms persist for more than 7 days
- symptoms clear up and occur again within a few days

If pregnant or breast-feeding, Ask a health professional before use

Keep out of reach of children. If swallowed, get medical help or contact a Poison Control Center right away.

Directions

Adult and Children 12 years of age and over

- Clean and dry affected area
- Remove film from patch and apply to the skin (see illustration)
- Apply one patch at a time to affected area, not more than 3 to 4 times daily
- Remove patch from the skin after at most 8-hour application

Children under 12 years of age: Consult a doctor

Other information

- Store at 68° - 77°F (20° - 25°C)
- Store in a cool dry place away from direct sunlight

Inactive Ingredients

Dihydroxyaluminium Aminoacetate, Edetate Disodium, Glycerin, Hydroxyacetophenone, Kaolin, L(+)- Tartaric Acid, Mineral oil, Polysorbate 80, Polyacrylic Acid, Polyvinylpyrrolidone K90, Propylene Glycol, Sodium Polyacrylate, Titanium Dioxide, Water